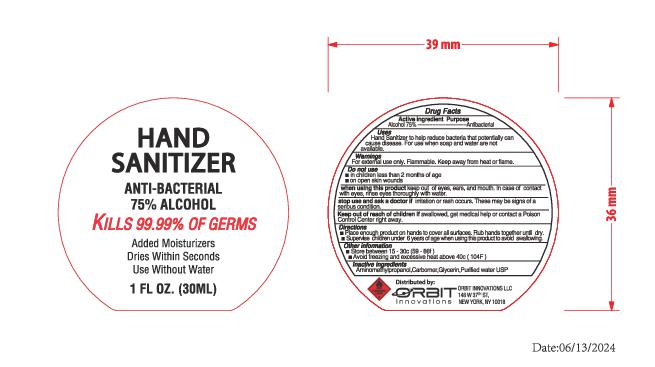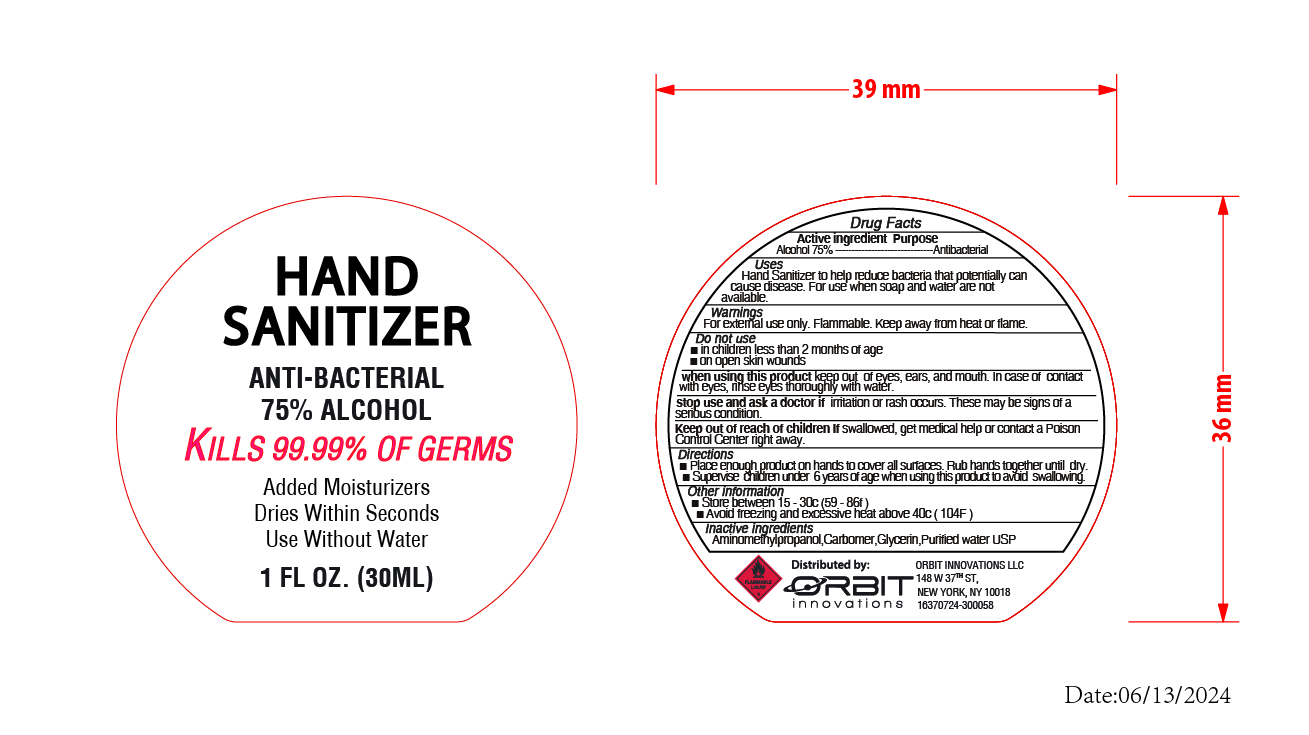 DRUG LABEL: ORBIT INNOVATIONS HAND SANITIZER
NDC: 73928-040 | Form: GEL
Manufacturer: Kingkey MBC Life Technology Group Co.,Ltd
Category: otc | Type: HUMAN OTC DRUG LABEL
Date: 20251211

ACTIVE INGREDIENTS: ALCOHOL 75 mL/100 mL
INACTIVE INGREDIENTS: AMINOMETHYLPROPANOL; CARBOMER 980; GLYCERIN; WATER

Active ingredient

Alcohol 75% ------------------------------- Antibacterial

Purpose

Anti-Bacterial

Uses

Effective in eliminating harmful germs and bacteria when soap and water are unavailable

Users

Effective in eliminating harmful germs and bacteria when soap and water are unavailable.

Warnings

For external use only. Flammable.Keep away from fire or flames.

Do not use

- In children less than 2 months of age
- on open skin wounds

When using this productdo not use in or near the eyes. In case of eye contact, flush eyes thoroughly with water.

Stop use and ask a doctor ifirritation and redness develops and lasts more than 72 hours.

Keep out of reach of children. If swallowed, get medical help or contact a Poison Control Center right away.

Keep out of reach of children. If swallowed, get medical help or contact a Poison Control Center right away.

Directions

- Place enough product in palm to thoroughly cover hands.Rub hands together briskly until dry.
- Supervise children under 6 years of age when using this product to avoid swallowing.

Other information

Store between 15 - 30c (59 - 86f)

Avoid freezing and excessive heat above 40c (104F)

Inactives ingredient

Aminomethylpropanol, Carbomer, Glycerin, Purified water USP